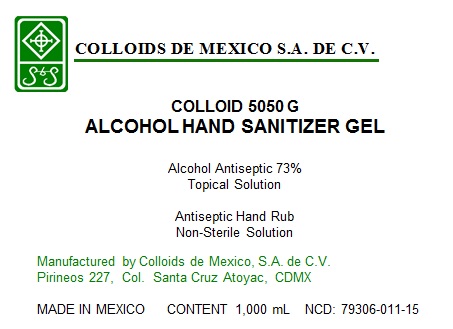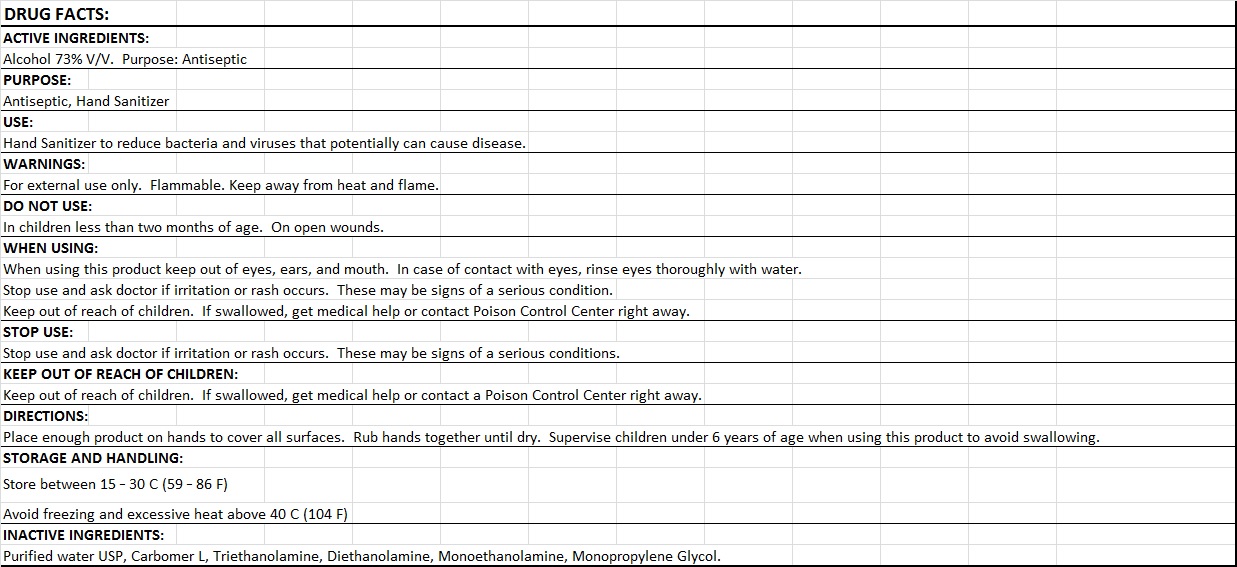 DRUG LABEL: COLLOID 5050 G
NDC: 79306-011 | Form: GEL
Manufacturer: COLLOIDS DE MEXICO, S.A. DE C.V.
Category: otc | Type: HUMAN OTC DRUG LABEL
Date: 20200804

ACTIVE INGREDIENTS: ALCOHOL 610.28 g/836 g
INACTIVE INGREDIENTS: CARBOMER HOMOPOLYMER TYPE C 58.52 g/836 g; PROPYLENE GLYCOL 25.08 g/836 g; MONOETHANOLAMINE 0.03344 g/836 g; DIETHANOLAMINE 0.96976 g/836 g; WATER 135.432 g/836 g; TROLAMINE 58.52 g/836 g

ACTIVE INGREDIENT

Alcohol 73% v/v. Purpose: Antiseptic.

Purpose

Antiseptic, Hand Sanitizer

Use

Hand Sanitizer to help reduce bacteria tht potentially can cause disease. For use when soap and water are not available.

Warnings

For external use only. Flammable. Keep away from flame.

Do not use

- In children less than 2 months of age.
- On open skin wounds.

When using this product keep out of eyes, ears and mouth. In case of contact with eyes, rinse eyes thoroughly with water.

Stop use and ask doctor if irritation or rash occurs. These may be signs of a serious condition.

Keep out of reach of children. If swallowed, get medical help or contact a Poison Control Center right away.

Stop use and ask a doctor if irritation accurs. These may be signs of a serious condition.

Keep out of reach of children. If swallowed, get medical help or contact a Poison Control Center right away.

DOSAGE AND ADMINISTRATION

Place enough product on hands to cover all surfaces. Rub hands together until dry.

Supervise children under 6 years of age when using this product to avoid swallowing.

STORAGE AND HANDLING

Store between 15-30C (59-86F)

Avoid freezing and excesive heat above 40C (104F)

INACTIVE INGREDIENT

Purified water USP, Carbomer L, Triethanolamine, Diethanolamine, Monoethanolamine, Monopropylene Glycol.